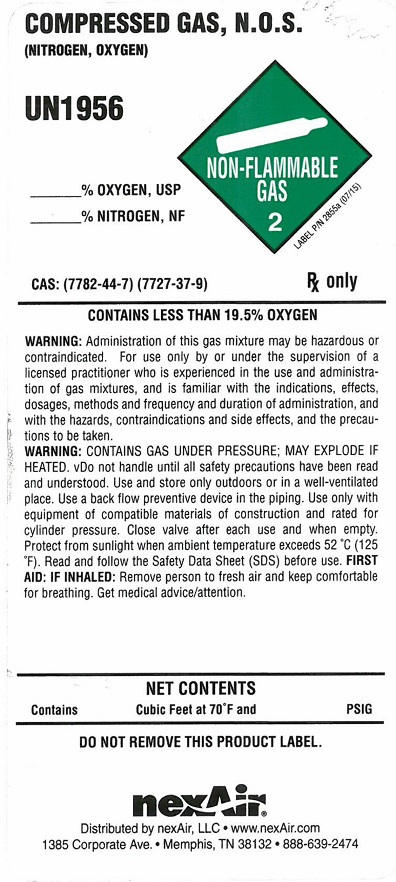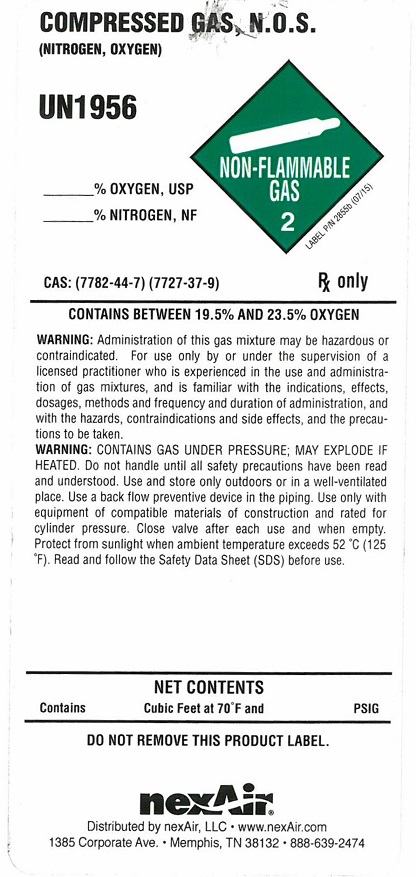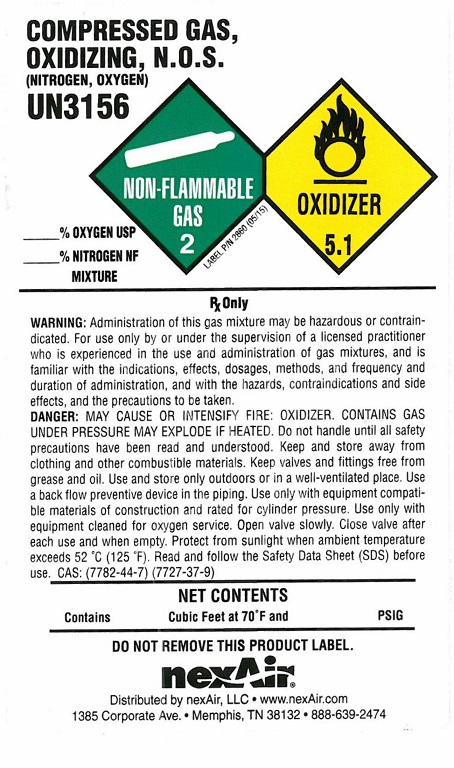 DRUG LABEL: Nitrogen Oxygen Mix
NDC: 12213-733 | Form: GAS
Manufacturer: NexAir, LLC
Category: prescription | Type: HUMAN PRESCRIPTION DRUG LABEL
Date: 20251031

ACTIVE INGREDIENTS: OXYGEN 210 mL/1 L
INACTIVE INGREDIENTS: NITROGEN 790 mL/1 L

Nitrogen Oxygen Mix Label

PACKAGE LABEL

COMPRESSED GAS, N.O.S. (NITROGEN, OXYGEN) UN1956
% OXYGEN USP % NITROGEN NF MIXTURE NON-FLAMMABLE GAS 2
CAS: OXYGEN (7782-44-7) (7727-37-9)
Rx only CONTAINS LESS THAN 19.5%
WARNING: Administration of this gas mixture may be hazardous or contraindicated. For use only by or under the supervision of a licensed practitioner who is experienced in the use and administration of gas mixtures and is familiar with the indications, effects, dosages, methods, and frequency and duration of administration, and with the hazards, contraindications, and side effects and the precautions to be taken.
DANGER: MAY CAUSE OR INTENSIFY FIRE; OXYDIZER. CONTAINS GAS UNDER PRESSURE; MAY EXPLODE IF HEATED. Do not handle until all safety precautions have been read and understood. Keep and store away from clothing and other combustible materials. Keep valves and fittings free from grease and oil. Use and store only outdoors or in a well-ventilated place. In case of fire: Stop leak if safe to do so. Use a back flow preventive device in the piping. Use only with equipment of compatible materials of construction and rated for cylinder pressure. Use only with equipment cleaned for oxygen service. Open valve slowly. Close valve after each use and when empty. Protect from sunlight when Protect from sunlight when ambient temperature exceeds 52 degrees C (125 degrees F). Read and follow the Safety Data Sheet (SDS) before use. FIRST AID: IF INHALED: Remove person to fresh air and keep comfortable bor breathing. Get medical advice/attention.
NET CONTENTS Contains Cubic Feet at 70 degrees F and PSIG
DO NOT REMOVE THIS PRODUCT LABEL
nexAir
Distributed by nexAir, LLC . www.nexAir.com
1385 Corporate Ave. . Memphis, TN 38132 . 888-639-2474

PACKAGE LABEL

COMPRESSED GAS, N.O.S. (NITROGEN, OXYGEN) UN1956
% OXYGEN USP % NITROGEN NF MIXTURE NON-FLAMMABLE GAS 2
CAS: OXYGEN (7782-44-7) (7727-37-9)
Rx only CONTAINS BETWEEN 19.5% and 23.5% OXYGEN
WARNING: Administration of this gas mixture may be hazardous or contraindicated. For use only by or under the supervision of a licensed practitioner who is experienced in the use and administration of gas mixtures and is familiar with the indications, effects, dosages, methods, and frequency and duration of administration, and with the hazards, contraindications, and side effects and the precautions to be taken.
DANGER: MAY CAUSE OR INTENSIFY FIRE; OXYDIZER. CONTAINS GAS UNDER PRESSURE; MAY EXPLODE IF HEATED. Do not handle until all safety precautions have been read and understood. Keep and store away from clothing and other combustible materials. Keep valves and fittings free from grease and oil. Use and store only outdoors or in a well-ventilated place. In case of fire: Stop leak if safe to do so. Use a back flow preventive device in the piping. Use only with equipment of compatible materials of construction and rated for cylinder pressure. Use only with equipment cleaned for oxygen service. Open valve slowly. Close valve after each use and when empty. Protect from sunlight when Protect from sunlight when ambient temperature exceeds 52 degrees C (125 degrees F). Read and follow the Safety Data Sheet (SDS) before use.
NET CONTENTS Contains Cubic Feet at 70 degrees F and PSIG
DO NOT REMOVE THIS PRODUCT LABEL
nexAir
Distributed by nexAir, LLC . www.nexAir.com
1385 Corporate Ave. . Memphis, TN 38132 . 888-639-2474